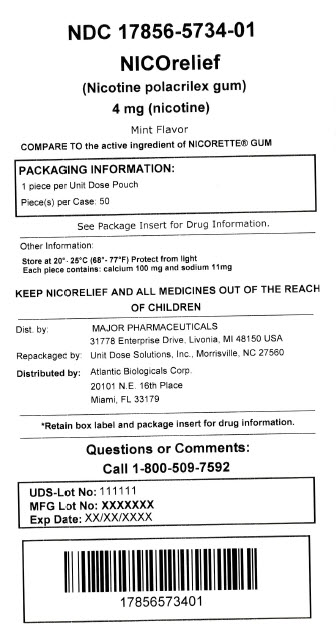 DRUG LABEL: Nicorelief
NDC: 17856-5734 | Form: GUM, CHEWING
Manufacturer: ATLANTIC BIOLOGICALS CORP.
Category: otc | Type: HUMAN OTC DRUG LABEL
Date: 20160920

ACTIVE INGREDIENTS: NICOTINE 4 mg/1 1
INACTIVE INGREDIENTS: POLACRILIN; ACESULFAME POTASSIUM; CALCIUM CARBONATE; CARNAUBA WAX; D&C YELLOW NO. 10; SODIUM BICARBONATE; SODIUM CARBONATE; SORBITOL; TALC

Major Pharmaceuticals Nicorelief® Drug Facts

Active ingredient (in each chewing piece)

Nicotine polacrilex (equal to 4 mg nicotine)

Purpose

Stop smoking aid

Use

- reduces withdrawal symptoms, including nicotine craving, associated with quitting smoking

Warnings

If you are pregnant or breast-feeding,

only use this medicine on the advice of your health care provider. Smoking can seriously harm your child. Try to stop smoking without using any nicotine replacement medicine. This medicine is believed to be safer than smoking. However, the risks to your child from this medicine are not fully known.

Ask a doctor before use if you have

- a sodium-restricted diet
- heart disease, recent heart attack, or irregular heartbeat. Nicotine can increase your heart rate.
- high blood pressure not controlled with medication. Nicotine can increase blood pressure.
- stomach ulcer or diabetes

Ask a doctor or pharmacist before use if you are

- using a non-nicotine stop smoking drug
- taking prescription medicine for depression or asthma. Your prescription dose may need to be adjusted.

Stop use and ask a doctor if

- mouth, teeth or jaw problems occur
- irregular heartbeat or palpitations occur
- you get symptoms of nicotine overdose such as nausea, vomiting, dizziness, diarrhea, weakness and rapid heartbeat
- you have symptoms of an allergic reaction (such as difficulty breathing or rash)

Keep out of reach of children and pets.

Pieces of nicotine gum may have enough nicotine to make children and pets sick. Wrap used pieces of gum in paper and throw away in the trash. In case of overdose, get medical help or contact a Poison Control Center right away (1-800-222-1222).

Directions

- if you are under 18 years of age, ask a doctor before use
- before using this product, read the enclosed User’s Guide for complete directions and other important information
- begin using the gum on your quit day
- if you smoke your first cigarette more than 30 minutes after waking up, use Nicotine Polacrilex Gum, 2 mg
- if you smoke your first cigarette within 30 minutes of waking up, use Nicotine Polacrilex Gum, 4 mg according to the following 12 week schedule:

Weeks 1 to 6 | Weeks 7 to 9 | Weeks 10 to 12
1 piece every; 1 to 2 hours | 1 piece every; 2 to 4 hours | 1 piece every; 4 to 8 hours

- nicotine gum is a medicine and must be used a certain way to get the best results
- chew the gum slowly until it tingles. Then park it between your cheek and gum. When the tingle is gone, begin chewing again, until the tingle returns.
- repeat this process until most of the tingle is gone (about 30 minutes)
- do not eat or drink for 15 minutes before chewing the nicotine gum, or while chewing a piece
- to improve your chances of quitting, use at least 9 pieces per day for the first 6 weeks
- if you experience strong or frequent cravings, you may use a second piece within the hour. However, do not continuously use one piece after another since this may cause you hiccups, heartburn, nausea or other side effects.
- do not use more than 24 pieces a day
- it is important to complete treatment. If you feel you need to use the gum for a longer period to keep from smoking, talk to your health care provider.

Other information

- each piece contains: calcium 100 mg and sodium 11 mg
- store at 20-25°C (68-77°F)
- protect from light

Inactive ingredients

acesulfame potassium, calcium carbonate, carnauba wax, D&C yellow no. 10, flavors, gum base, sodium bicarbonate, sodium carbonate anhydrous, sorbitol, talc

Questions or comments?

call 1-866-677-7858

Principal Display Panel

COMPARE TO the active ingredient of NICORETTE® GUM

NEW DIRECTIONS FOR USE

Keep Using if You Slip Up and Have a Cigarette

Use Beyond 12 Weeks if Needed to Quit

NICOrelief®

nicotine polacrilex gum, USP, 4 mg (nicotine)

Stop Smoking Aid

FOR THOSE WHO SMOKE THEIR FIRST CIGARETTE WITHIN 30 MINUTES OF WAKING UP.

If you smoke your first cigarette MORE THAN 30 MINUTES after waking up, use NICOrelief®, Nicotine Polacrilex Gum, 2 mg

mint flavor

4mg

50 Pieces

actual size

Includes User’s Guide

Free Audio CD upon request. See inside.